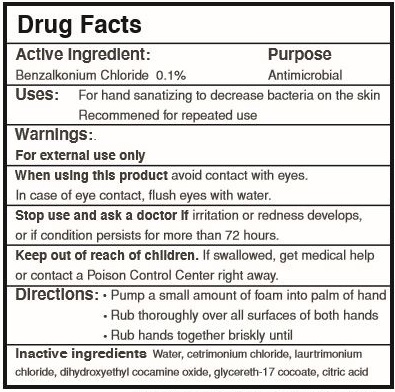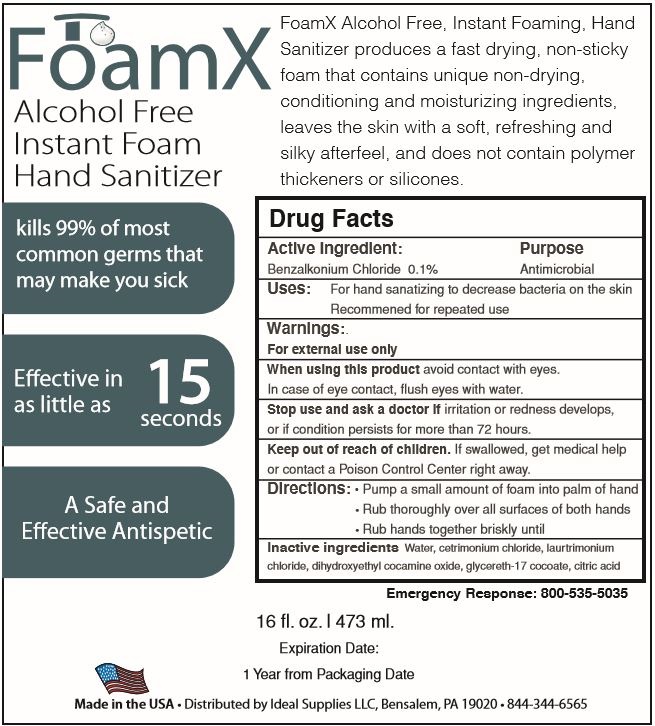 DRUG LABEL: Foam - X
NDC: 74407-011 | Form: LIQUID
Manufacturer: Ideal Supplies, LLC
Category: otc | Type: HUMAN OTC DRUG LABEL
Date: 20221025

ACTIVE INGREDIENTS: BENZALKONIUM CHLORIDE 0.13 mg/1 mL
INACTIVE INGREDIENTS: DIHYDROXYETHYL COCAMINE OXIDE; WATER; GLYCERETH-17 COCOATE; ANHYDROUS CITRIC ACID; LAURTRIMONIUM CHLORIDE; CETRIMONIUM CHLORIDE

ACTIVE Ingredients

Dosage

Inactive

WARNINGS

Warninng

Indication & Usage

Purpose Section

Label